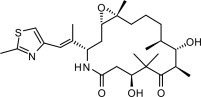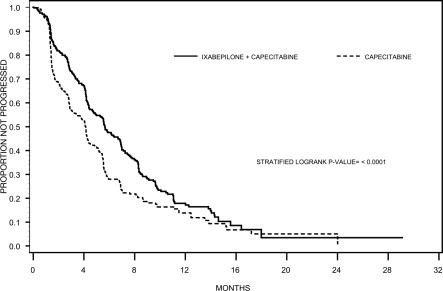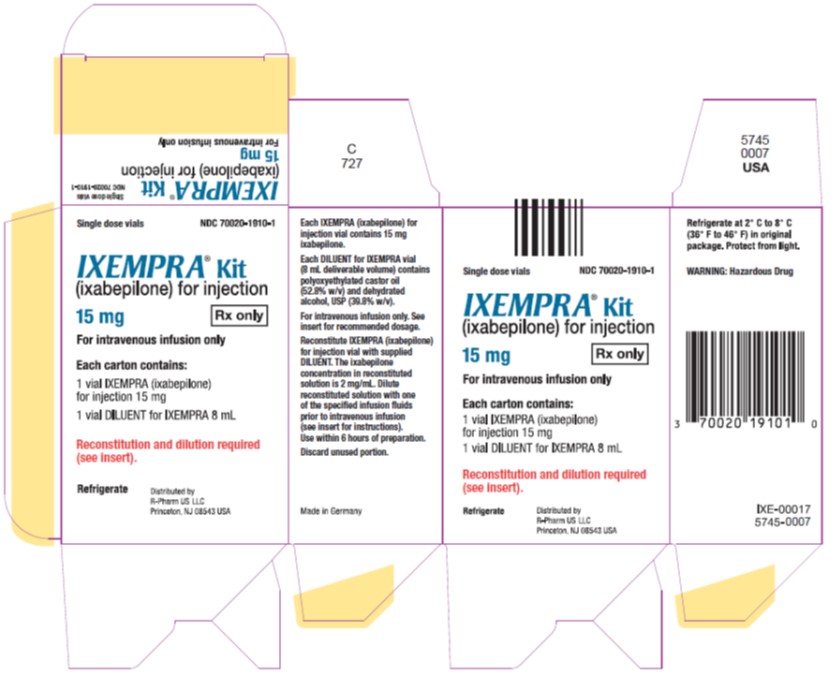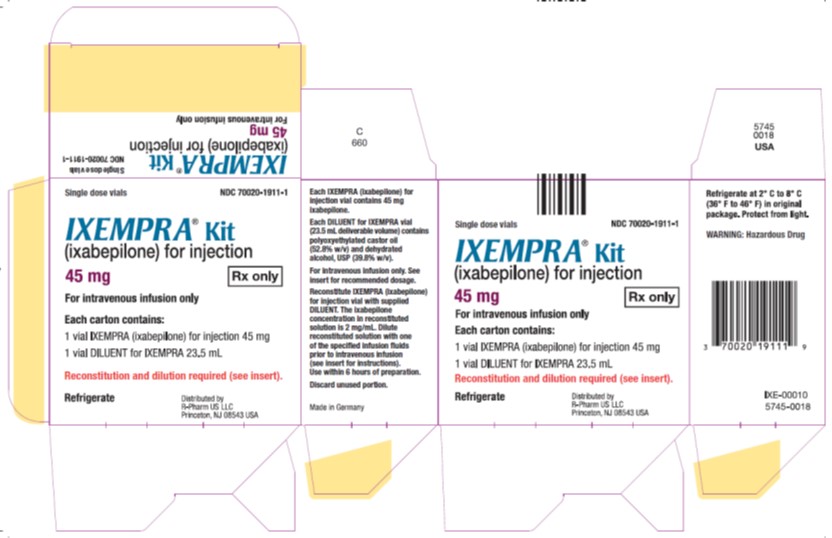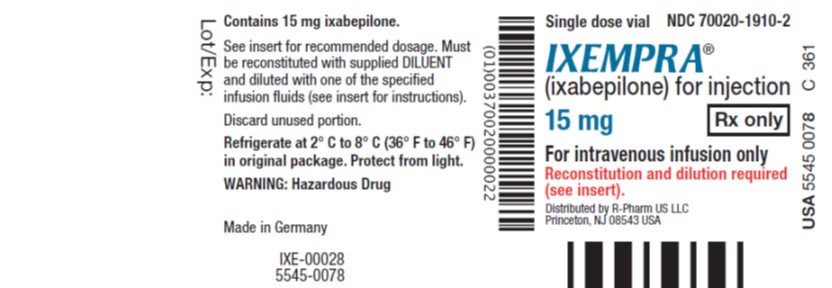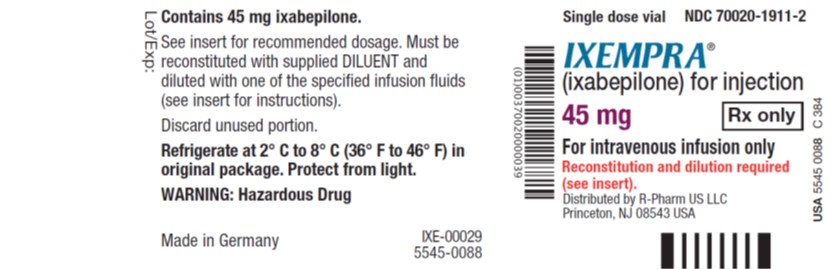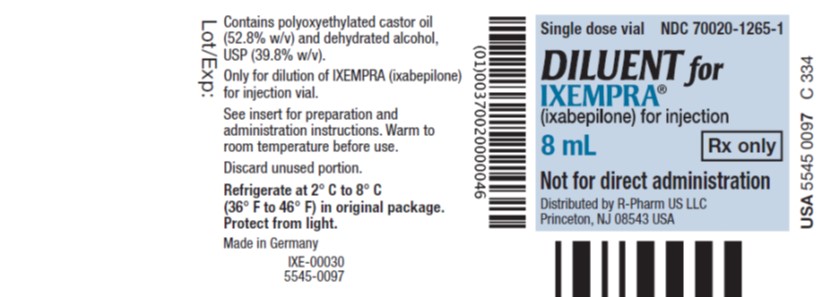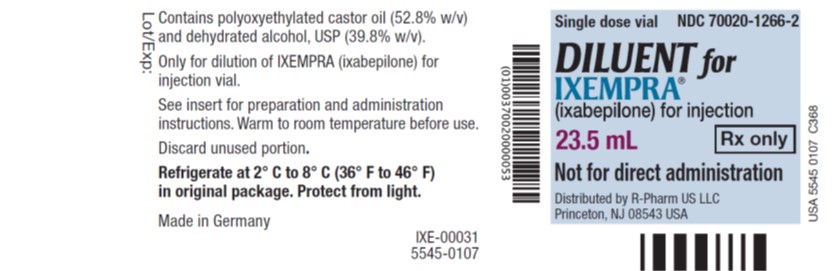 DRUG LABEL: IXEMPRA
NDC: 70020-1910 | Form: KIT | Route: INTRAVENOUS
Manufacturer: R-Pharm US Operating, LLC
Category: prescription | Type: HUMAN PRESCRIPTION DRUG LABEL
Date: 20251204

ACTIVE INGREDIENTS: IXABEPILONE 15 mg/15 mg
INACTIVE INGREDIENTS: POLYOXYL 35 CASTOR OIL; ALCOHOL

HIGHLIGHTS OF PRESCRIBING INFORMATION

These highlights do not include all the information needed to use IXEMPRA® safely and effectively. See full prescribing information for IXEMPRA®.
IXEMPRA® Kit (ixabepilone) for Injection, for intravenous infusion only
Initial U.S. Approval: 2007

WARNING: TOXICITY IN PATIENTS WITH HEPATIC IMPAIRMENT

See full prescribing information for complete boxed warning.

IXEMPRA® in combination with capecitabine is contraindicated in patients with AST or ALT >2.5 x ULN or bilirubin >1 x ULN due to increased risk of toxicity and neutropenia-related death. (4, 5.3)

1 INDICATIONS AND USAGE

IXEMPRA is a microtubule inhibitor indicated for treatment:

- In combination with capecitabine for patients with metastatic or locally advanced breast cancer resistant to treatment with an anthracycline and a taxane, or whose cancer is taxane resistant and for whom further anthracycline therapy is contraindicated. (1).
- As a single agent for patients with metastatic or locally advanced breast cancer after failure of an anthracycline, a taxane, and capecitabine. (1).

2 DOSAGE AND ADMINISTRATION

- The recommended dosage of IXEMPRA is 40 mg/m^2 administered as a 3-hour intravenous infusion once every 3 weeks (2.2).

Dose reduction is required in patients with elevated AST, ALT, or bilirubin.(2.3, 8.6)

- IXEMPRA must be reconstituted with the supplied DILUENT and further diluted to a concentration of 0.2 mg/mL to 0.6 mg/mL prior to administration (2.6).

3 DOSAGE FORMS AND STRENGTHS

- IXEMPRA for injection, 15 mg supplied with DILUENT for IXEMPRA, 8 mL (3)
- IXEMPRA for injection, 45 mg supplied with DILUENT for IXEMPRA, 23.5 mL (3)

4 CONTRAINDICATIONS

- Baseline neutrophil count <1500 cells/mm^3 or a platelet count <100,000 cells/mm^3 (4).
- Hypersensitivity to drugs formulated with Cremophor® EL (4).
- IXEMPRA in combination with capecitabine is contraindicated for use in patients with AST or ALT >2.5 x ULN or bilirubin >1 x ULN.(4).

5 WARNINGS AND PRECAUTIONS

- Peripheral Neuropathy: Monitor for symptoms of neuropathy (sensory and motor neuropathy).) Withhold, reduce, or discontinue IXEMPRA depending on severity. (2.3, 5.1).
- Myelosuppression: Neutropenia, febrile neutropenia, and infections have occurred. Monitor blood cell counts before and during treatment with IXEMPRA. Withhold, reduce, or discontinue IXEMPRA depending on severity (2.3, 5.2).
- Increased Toxicity in Patients with Hepatic Impairment: Grade 4 neutropenia, febrile neutropenia, and serious adverse reactions may occur in patients with hepatic impairment during treatment with IXEMPRA. Reduce dose depending on severity. (2.3, 5.3, 6.1).
- Hypersensitivity Reactions: Severe hypersensitivity reactions (including anaphylaxis) have occurred. Premedicate all patients before treatment with IXEMPRA. Withhold, reduce, or discontinue IXEMPRA depending on severity (2.1, 2.3, 5.4).
- Cardiac Adverse Reactions: Myocardial ischemia and ventricular dysfunction have occurred. Closely monitor patients with a history of cardiac disease during treatment with IXEMPRA. Consider discontinuation of IXEMPRA in patients who develop cardiac ischemia or impaired cardiac function (2.3, 5.5).
- Embryo-Fetal Toxicity: Can cause fetal harm. Advise patients of potential risk to a fetus and to use effective contraception (5.6, 8.1, 8.3)
- Alcohol Content: The alcohol content in a dose of IXEMPRA may affect the central nervous system. This may include impairment of a patient's ability to drive or use machines immediately after infusion. (5.7).

6 ADVERSE REACTIONS

- The most common adverse reactions (≥20%) are peripheral sensory neuropathy, fatigue/asthenia, myalgia/arthralgia, alopecia, nausea, vomiting, stomatitis/mucositis, diarrhea, and musculoskeletal pain. Additional reactions occurred in ≥20% in combination treatment: palmar-plantar erythrodysesthesia syndrome, anorexia, abdominal pain, nail disorder, and constipation (6).
- Hematologic laboratory abnormalities (>40%) include neutropenia, leukopenia, anemia, and thrombocytopenia (6).

To report SUSPECTED ADVERSE REACTIONS, contact R-Pharm US at 1-844-586-8953 or FDA at 1-800-FDA-1088 or www.fda.gov/medwatch

7 DRUG INTERACTIONS

Strong CYP3A4 Inhibitors:

- Avoid strong CYP3A4 inhibitors. If coadministration cannot be avoided, reduce the dosage of IXEMPRA (2.5, 7.1).

Strong CYP3A4 Inducers:

- Avoid strong CYP3A4 inducers. If coadministration cannot be avoided, reduce the dosage of IXEMPRA (2.5, 7.1).

8 USE IN SPECIFIC POPULATIONS

- Lactation: Advise not to breastfeed (8.2).
- Hepatic Impairment: Reduce the dosage in patients with elevated AST, ALT, or bilirubin (2.4, 8.6).

FULL PRESCRIBING INFORMATION

WARNING: TOXICITY IN PATIENTS WITH HEPATIC IMPAIRMENT

IXEMPRA in combination with capecitabine is contraindicated in patients with AST or ALT >2.5 x ULN or bilirubin >1 x ULN due to increased risk of toxicity and neutropenia-related death [see Contraindications (4) and Warnings and Precautions (5.3)].

1 INDICATIONS AND USAGE

IXEMPRA is indicated in combination with capecitabine for the treatment of patients with metastatic or locally advanced breast cancer resistant to treatment with an anthracycline and a taxane, or whose cancer is taxane resistant and for whom further anthracycline therapy is contraindicated. Anthracycline resistance is defined as progression while on therapy or within 6 months in the adjuvant setting or 3 months in the metastatic setting. Taxane resistance is defined as progression while on therapy or within 12 months in the adjuvant setting or 4 months in the metastatic setting [see Clinical Studies (14)].

IXEMPRA is indicated as a single agent for the treatment of patients with metastatic or locally advanced breast cancer whose tumors are resistant or refractory to anthracyclines, taxanes, and capecitabine [see Clinical Studies (14)].

2 DOSAGE AND ADMINISTRATION

2.1 Premedication

All patients must be premedicated approximately 1 hour before the infusion of IXEMPRA with:

- An H1 antagonist (eg, diphenhydramine 50 mg orally or equivalent) and
- An H2 antagonist (eg, ranitidine 150 - 300 mg orally or equivalent).

Patients who experienced a hypersensitivity reaction to IXEMPRA require premedication with corticosteroids (eg, dexamethasone 20 mg intravenously, 30 minutes before infusion or orally, 60 minutes before infusion) in addition to pretreatment with H1 and H2 antagonists [see Warnings and Precautions (5.4)].

2.2 Recommended Dosage

The recommended dosage of IXEMPRA is 40 mg/m^2 administered intravenously over 3 hours every 3 weeks. Calculate doses for patients with body surface area (BSA) greater than 2.2 m^2 should be calculated based on 2.2 m^2.

2.3 Dosage Modification for Adverse Reactions

Evaluate patients during treatment by periodic clinical observation and laboratory tests including complete blood cell counts [see the Warnings and Precautions (5)].

Dosage modifications for IXEMPRA for adverse reactions are shown in Table 1.

If adverse reactions recur, reduce dose by an additional 20%.

Re-treatment Criteria:

Determine dosage modifications at the start of each cycle based on nonhematologic toxicity or blood counts from the preceding cycle following the guidelines in Table 1. Do not begin a new cycle of treatment unless the neutrophil count is at least 1500 cells/mm^3, the platelet count is at least 100,000 cells/mm^3 [see Contraindictions]. Withhold IXEMPRA until nonhematologic toxicities have improved to grade 1 (mild) or resolved prior to beginning a new cycle of treatment.

Evaluate patients during treatment by periodic clinical observation and laboratory tests including complete blood cell counts [see the Warnings and Precautions (5)]. Dosage modifications for IXEMPRA for adverse reactions are shown in Table 1. If adverse reactions recur, reduce dose by an additional 20%.

Table 1: Dosage for Modification for Adverse Reactionsa
IXEMPRA | IXEMPRA
(Single Agent or Combination Therapy) | Dosage Modification
Nonhematologic:
Grade 2 neuropathy (moderate) lasting ≥7 days | Decrease the dose by 20%
Grade 3 neuropathy (severe) lasting <7 days | Decrease the dose by 20%
Grade 3 neuropathy (severe) lasting ≥7 days or disabling neuropathy | Discontinue treatment
Any grade 3 toxicity (severe) other than neuropathy | Decrease the dose by 20%
Transient grade 3 arthralgia/myalgia or fatigue | No change in dose of IXEMPRA
Grade 3 hand-foot syndrome (palmar-plantar erythrodysesthesia)
Any grade 4 toxicity (disabling) | Discontinue treatment
Hematologic:
Neutrophil <500 cells/mm^3 for ≥7 days | Decrease the dose by 20%
Febrile neutropenia | Decrease the dose by 20%
Platelets <25,000/mm^3 or platelets <50,000/mm^3 with bleeding | Decrease the dose by 20%
Capecitabine | Capecitabine
(when used in combination with DCEMPRA) | Dosage Modification
Nonhematologic: | See capecitabine prescribing information
Hematologic:
Platelets <25,000/mm^3 or <50,000/mm^3 with bleeding | Hold for concurrent diarrhea or
 | stomatitis until platelet count >50,000/mm^3,
 | then continue at same dose.
Neutrophils <500 cells/mm^3 for ≥7 days or febrile neutropenia | Hold for concurrent diarrhea or
 | stomatitis until neutrophil count >1,000 cells/mm^3,
 | then continue at same dose.
aToxicities graded in accordance with National Cancer Institute (NCI) Common Terminology Criteria for Adverse Events(CTCAE v3.0).

Combination Therapy:

IXEMPRA in combination with capecitabine is contraindicated in patients with AST or ALT >2.5 x ULN or bilirubin >1 x ULN. Patients receiving combination treatment who have AST and ALT ≤2.5 x ULN and bilirubin ≤1 x ULN [see Contraindictions (4)].

2.4 Dosage Modifications in Patients with Hepatic Impairment

Dosage Modifications in Patients with Hepatic Impairment

Combination Therapy

IXEMPRA in combination with capecitabine is contraindicated in patients with AST or ALT >2.5 x ULN or bilirubin >1 x ULN [see Contraindications (4)].

Single Agent

Reduce the dose of IXEMPRA for patients with hepaptic impairment as recommended in Table 2. [see Warnings and Precautions (5.3) and Use in Specific Populations (8.6)].

Table 2: Dose Modifications for IXEMPRA as a Single Agent for Patients with Hepatic Impairment
 | Transaminase Levels |  | Bilirubin Levelsa | IXEMPRAb (mg/m^2
 | AST and ALT ≤2.5 x ULN | and | ≤1 x ULN | No Modification
 | AST and ALT ≤10x ULN | and | ≤1.5 x ULN | 32
 | AST and ALT ≤10 x ULN | and | >1.5 to ≤3 x ULN | 20-30 c
 | AST and ALT > 10 x ULN | or | >3 x ULN | Avoid Use
a Excluding patients whose total bilirubin is elevated due to Gilbert's disease.
b Dosage recommendations are for first course of therapy; further decreases in subsequent courses should be based on individual tolerance.
c For patients with AST and ALT ≤ 10x ULN and lilirubin >1.5 to 3x ULN, consider increasing the dose from 20mg/m^2 to 30mg/m^2 in subsequent cycles if a dose of 20 mg/m^2 is tolerated.

2.5 Dosage Modification for Drug Interactions

Strong CYP3A4 Inhibitors

Avoid the use of concomitant use of strong CYP3A4 inhibitors. If coadministration of a strong CYP3A4 inhibitor with IXEMPRA cannot be avoided, reduce the dose of IXEMPRA to 20 mg/m^2. If the strong inhibitor is discontinued, increase the IXEMPRA dose (at 1 week after discontinuing the inhibitor) to that was used before starting the strong inhibitor [see Clinical Pharmacology (12.3)].

Strong CYP3A4 Inducers

Avoid the concomitant use of strong CYP3A4 inducers. If coadministration of a strong CYP3A4 inducer with IXEMPRA cannot be avoided, gradually increase the dose from 40 mg/m2 to 60 mg/m^2 as tolerated once a patient has been maintained on a strong CYP3A4 inducer. Administer IXEMPRA as a 4-hour intravenous infusion and monitor patients carefully for adverse reactions.

If the strong inducer is discontinued, reduce the IXEMPRA dose to that before that before starting the strong CYP3A4 inducer [see Clinical Pharmacology (12.3)].

2.6 Preparation and Administration

IXEMPRA is a hazardous drug. Follow aplicable special handling and disposal procedures.^1

IXEMPRA Kit contains two vials, a vial labeled IXEMPRA (ixabepilone) for injection which contains ixabepilone powder and a vial containing DILUENT for IXEMPRA. Use only the supplied DILUENT to reconstitute IXEMPRA (ixabepilone) for injection.

Reconstituation

1. Prior to reconstituting, remove the IXEMPRA Kit from the refrigerator and allow it to stand at room temperature for approximately 30 minutes. When the vials are first removed from the refrigerator, a white precipitate may be observed in the DILUENT vial. This precipitate will dissolve to form a clear solution once the DILUENT warms to room temperature.

2. With a suitable syringe, aseptically withdraw the DILUENT and slowly inject it into the IXEMPRA for injection vial. The 15-mg IXEMPRA is reconstituted with 8 mL of DILUENT and the 45-mg IXEMPRA is reconstituted with 23.5 mL of DILUENT.

3. Gently swirl and invert the vial until the powder in IXEMPRA is completely dissolved.

4. After reconstituting with the DILUENT, the concentration of ixabepilone is 2 mg/mL.

5. After reconstituting IXEMPRA, dilute the reconstituted with infusion fluid as soon as possible. The reconstituted solution may be stored in the vial (not the syringe) for a maximum of 1 hour at room temperature and room light.

Dilution

Before administration, the reconstituted solution must be further diluted with one of the specified infusion fluids listed below. Other infusion fluids should not be used with IXEMPRA.

The IXEMPRA infusion must be prepared in a DEHP [di-(2-ethylhexyl) phthalate] free bag.

The following infusion fluids have been qualified for use in the dilution of IXEMPRA:

Lactated Ringer’s Injection, USP

0.9% Sodium Chloride Injection, USP (pH adjusted with Sodium Bicarbonate Injection, USP)

When using a 250 mL or a 500 mL bag of 0.9% Sodium Chloride Injection to prepare the infusion, the pH must be adjusted to a pH between 6.0 and 9.0 by adding 2 mEq (ie, 2 mL of an 8.4% w/v solution or 4 mL of a 4.2% w/v solution) of Sodium Bicarbonate Injection, prior to the addition of the reconstituted IXEMPRA solution.

- PLASMA-LYTE A Injection pH 7.4®

For most doses, a 250 mL bag of infusion fluid is sufficient. However, it is necessary to check the final IXEMPRA infusion concentration of each dose based on the volume of infusion fluid to be used.

The final concentration for infusion must be between 0.2 mg/mL and 0.6 mg/mL. To calculate the final infusion concentration, use the following formulas:

Total Infusion Volume = mL of Reconstituted Solution + mL of infusion fluid

Final Infusion Concentration = Dose of IXEMPRA (mg)/Total Infusion Volume (mL)

1. Aseptically, withdraw the appropriate volume of reconstituted solution containing 2 mg of ixabepilone per mL.

2. Aseptically, transfer to an intravenous bag containing an appropriate volume of infusion fluid to achieve the final desired concentration of IXEMPRA.

3. Thoroughly mix the infusion bag by manual rotation.

4. Once diluted with infusion fluid, the solution is stable at room temperature and room light for a maximum of 6 hours. Administration of diluted IXEMPRA must be completed within this 6-hour period.

Administration

The infusion solution must be administered through an appropriate in-line filter with a microporous membrane of 0.2 to 1.2 microns.

DEHP-free infusion containers and administration sets must be used.

Discard any remaining solution according to institutional procedures for hazardous drugs.

3 DOSAGE FORMS AND STRENGTHS

IXEMPRA for injection, 15 mg single-dose vial supplied with DILUENT for IXEMPRA, 8 mL.

IXEMPRA for injection, 45 mg single-dose vial supplied with DILUENT for IXEMPRA, 23.5 mL.

4 CONTRAINDICATIONS

IXEMPRA is contraindicated in patients who have:

- a neutrophil count <1500 cells/mm ^3 or a platelet count <100,000 cells/mm ^3 [see Warnings and Precautions (5.2)].
- a history of severe hypersensitivity to agents containing Cremophor® EL or its derivatives (e.g., polyoxyethylated castor oil) [see Warnings and Precautions (5.4)].

IXEMPRA in combination with capecitabine is contraindicated in patients with AST or ALT >2.5 x ULN or bilirubin >1 x ULN [see Boxed Warning and Warnings and Precautions (5.3)].

5 WARNINGS AND PRECAUTIONS

5.2 Myelosuppression

Severe, life-threatening, or fatal myelosuppression can occur in patients treated with IXEMPRA. Myelosuppression is dose-dependent and primarily manifests as neutropenia. In clinical studies, grade 4 neutropenia (<500 cells/mm^3) occurred in 36% of patients treated with IXEMPRA in combination with capecitabine and 23% of patients treated with single agent IXEMPRA monotherapy. Febrile neutropenia and infection with neutropenia were reported in 5% and 6% of patients treated with IXEMPRA in combination with capecitabine, respectively, and 3% and 5% of patients treated with IXEMPRA as a single agent, respectively. Neutropenia-related death occurred in 1.9% of 414 patients with normal hepatic function or mild hepatic impairment treated with IXEMPRA in combination with capecitabine. The rate of neutropenia-related deaths was higher (29%, 5 out of 17) in patients with AST or ALT >2.5 x ULN or bilirubin >1.5 x ULN [see Boxed Warning, Contraindications (4), and Warnings and Precautions (5.3)]. Neutropenia-related death occurred in 0.4% of 240 patients treated with IXEMPRA as a single agent. No neutropenia-related deaths were reported in 24 patients with AST or ALT >2.5 x ULN or bilirubin >1.5 x ULN treated with IXEMPRA as a single agent.

IXEMPRA is contraindicated for use in patients with a neutrophil count of <1500 cells/mm^3. [see Contraindications (4)].

Monitor patients receiving IXEMPRA for myelosuppression with frequent peripheral blood cell counts. Withhold, reduce, or discontinue IXEMPRA depending on the severity and persistence of myelosuppression [see Dosage and Administration (2.3)].

5.1 Peripheral Neuropathy

Peripheral neuropathy (sensory and motor neuropathy) occurred in patients treated with IXEMPRA in combination with capecitabine and in patients treated with single agent IXEMPRA as shown in Table (see Table 3).

Table 3: Peripheral Neuropathy
 | IXEMPRA | IXEMPRA as
 | with capecitabine | Single Agent
 | Study 046 | Study 081
Peripheral neuropathy (all grades)a,b | 67% | 63%
Peripheral neuropathy (grades 3/4)a,b | 23% | 14%
Discontinuation due to neuropathy | 21% | 6%
Median number of cycles to onset of grade 3/4 neuropathy | 4 | 4
Median time to improvement of grade 3/4 neuropathy to baseline or to grade 1 | 6.0 weeks | 4.6 weeks
a Sensory and motor neuropathy combined.
b 24% and 27% of patients in 046 and 081, respectively, had preexisting neuropathy (grade 1).

In Studies 046 and 081, 80% and 87%, respectively, of patients with peripheral neuropathy who received IXEMPRA had improvement or no worsening of their neuropathy following dose reduction. For patients with grade 3 or 4 neuropathy in Studies 046 and 081, 76% and 79%, respectively, had documented improvement to baseline or grade 1, twelve weeks after onset.

A pooled analysis of 1540 cancer patients treated with IXEMPRA indicated that patients with diabetes mellitus or preexisting peripheral neuropathy may be at increased risk of severe neuropathy. Patients with moderate to severe neuropathy (grade 2 or greater) were excluded from studies with IXEMPRA.

Monitor patients for symptoms of neuropathy, such as burning sensation, hyperesthesia, hypoesthesia, paresthesia, discomfort, or neuropathic pain. Withhold, reduce, or discontinue IXEMPRA depending on the severity and persistence of peripheral neuropathy [ see Dosage and Administration (2.3)].

5.3 Increased Toxicities in Patients with Hepatic Impairment

Patients with baseline AST or ALT >2.5 x ULN or bilirubin >1.5 x ULN experienced greater toxicity than patients with baseline AST or ALT ≤2.5 x ULN or bilirubin ≤1.5 x ULN when treated with IXEMPRA at 40 mg/m^2 in combination with capecitabine or as single agent in breast cancer studies.

In combination with capecitabine, the overall frequency of grade 3/4 adverse reactions, febrile neutropenia, serious adverse reactions, and toxicity-related deaths was increased oin patients with hepatic impairment. IXEMPRA in combination with capecitabine is contraindicated in patients with AST or ALT >2.5 x ULN or bilirubin >1 x ULN due to increased risk of toxicity- and neutropenia-related death [see Boxed Warning, Contraindications (4), and Warnings and Precautions (5.2)].

With IXEMPRA single agent therapy, grade 4 neutropenia, febrile neutropenia, and serious adverse reatcitons were increased in patients with hepatic impairment [see Warnings and Precautions (5.2) and Adverse Reactions (6.1). Reduce the dose IXEMPRA based in the degree of hepatic impairment. Avoid use in patients with AST or ALT >10 x ULN or bilirubin >3 x ULN [see Dosage and Administration (2.4)]

5.4 Hypersensitivity Reactions

IXEMPRA is contraindicated in patients with a history of a severe hypersensitivity reaction to agents containing Cremophor® EL or its derivatives (eg, polyoxyethylated castor oil) [ see Contraindications (4)].

Of the 1323 patients treated with IXEMPRA in clinical studies, 9 patients (1 %) had experienced severe hypersensitivity reactions (including anaphylaxis). Three of the 9 patients were able to be retreated. Patients who experience a hypersensitivity reaction in one cycle of IXEMPRA must be premedicated in subsequent cycles with a corticosteroid in addition to the H1 and H2 antagonists, and extension of the infusion time should be considered [see Dosage and Administration (2.3) and Contraindications (4)]

Administer an H1 and H2antagonist approximately 1 hour before IXEMPRA infusion and observe patients for hypersensitivity reaction occur, stop the infusion of IXEMPRA provide supportive treatment as clinically indicated (e.g.. epinephrine, corticosteriods).

5.5 Cardiac Adverse Reactions

Cardiac adverse reactions (myocardial ischemia and ventricular dysfunction) occurred in patients receiving IXEMPRA in combination with capecitabine (1.9%) and as a single agent (0.3%). Supraventricular arrhythmias were observed in the combination arm (0.5%).

Closely monitor patients with a history of cardiac disease during treatment with IXEMPRA. Consider discontinuation of IXEMPRA in patients who develop cardiac ischemia or impaired cardiac function [see Dosage and Administration (2.3)].

5.6 Embryo-Fetal Toxicity

Based on findings in animals and its mechanism of action, IXEMPRA can cause fetal harm when administered to a pregnant woman. In animal reproduction studies, intravenous administration of ixabepilone to pregnant rats and rabbits during the period of organogenesis caused maternal toxicity, embryo-fetal lethality, and fetal abnormalities at maternal exposures below the human clinical exposure based on AUC. Advise females of reproductive potential and pregnant women of the potential risk to a fetus. Advise females of reproductive potential to use effective contraception during treatment with IXEMPRA and for 7 months after the last dose. Advise male patients with female partners of reproductive potential to use effective contraception during treatment with IXEMPRA and for 4 months after the last dose [see Use in Specific Populations (8.1, 8.3) and Clinical Pharmacology (12.1)].

5.7 Alcohol Content

The alcohol content in a dose of IXEMPRA may affect the central nervous system and should be taken into account for patients in whom alcohol intake should be avoided or minimized. Consideration should be given to the alcohol content in IXEMPRA on the ability to drive or use machines immediately after the infusion. Each administration of IXEMPRA at the recommended dosage of 40 mg/m^2 delivers approximately 8.4 g/m^2 of ethanol. For a patient with a BSA of 2.0 m^2, this would deliver approximately 16.8 grams of ethanol [see Description (11)].

6 ADVERSE REACTIONS

The following adverse reactions are discussed in greater detail in other sections.

- Peripheral neuropathy [see Warnings and Precautions (5.1)]
- Myelosuppression [see Warnings and Precautions (5.2)]
- Hypersensitivity reactions [see Warnings and Precautions (5.4)]
- Cardiac Adverse reactions [see Warnings and Precautions (5.5)]

6.1 Clinical Trials Experience

Because clinical trials are conducted under widely varying conditions, the adverse reaction rates observed in the clinical trials of a drug cannot be directly compared to rates in other clinical trials and may not reflect the rates observed in clinical practice.

Unless otherwise specified, assessment of adverse reactions is based on one randomized study (Study 046) and one single-arm study (Study 081). In Study 046, 369 patients with metastatic breast cancer were treated with IXEMPRA 40 mg/m^2 administered intravenously over 3 hours every 21 days, combined with capecitabine 1000 mg/m^2 twice daily for 2 weeks followed by a 1-week rest period. Patients treated with capecitabine as a single agent (n=368) in this study received 1250 mg/m twice daily for 2 weeks every 21 days. In Study 081, 126 patients with metastatic or locally advanced breast cancer were treated with IXEMPRA 40 mg/m^2 administered intravenously over 3 hours every 3 weeks.

The most common adverse reactions (≥20%) reported by patients receiving IXEMPRA were peripheral sensory neuropathy, fatigue/asthenia, myalgia/arthralgia, alopecia, nausea, vomiting, stomatitis/mucositis, diarrhea, and musculoskeletal pain. The following additional reactions occurred in ≥20% in combination treatment: palmar-plantar erythrodysesthesia (hand-foot) syndrome, anorexia, abdominal pain, nail disorder, and constipation. The most common hematologic abnormalities (>40%) include neutropenia, leukopenia, anemia, and thrombocytopenia.

Table 4 presents nonhematologic adverse reactions reported in 5% or more of patients. Hematologic abnormalities are presented separately in Table 5.

Table 4 presents nonhematologic adverse reactions reported in 5% or more of patients. Hematologic abnormalities are presented separately in Table 5.

 |  |  | Study 046 |  | Study 081
 | IXEMPRA with capecitabine n=369 |  | Capecitabine n=368 |  | IXEMPRA Single Agent n=126
Adverse Reaction | All Grades | Grade 3/4 | All Grades | Grade 3/4 | All Grades | Grade 3/4
Preferred Term | (%) | (%) | (%) | (%) | (%) | (%)
Infections and Infestations
Upper respiratory tract infection | 4 | 0 | 3 | 0 | 6 | 0
Blood and Lymphatic System Disorders |  |  |  | 1d |  | 3d
Febrile neutropenia | 5 | 4c | 1 | 1d | 3 | 3d
Immune System Disorders |  |  |  |  |  | 1d
Hypersensitivityb | 2 | 1d | 0 | 0 | 5 | 1d
Metabolism and Nutrition Disorders
Anorexiab | 34 | 3d | 15 | 1d | 19 | 2d
Dehydrationb | 5 | 2 | 2 | <1d | 2 | 1d
Psychiatric Disorders
Insomniab | 9 | <1d | 2 | 0 | 5 | 0
Nervous System Disorders Peripheral neuropathy
Sensory neuropathyb | 65 | 21 | 16 | 0 | 62 | 14
Motor neuropathyb | 16 | 5d | <1 | 0 | 10 | 1d
Headache | 8 | <1d | 3 | 0 | 11 | 0
Taste disorderb | 12 | 0 | 4 | 0 | 6 | 0
Dizziness | 8 | 1d | 5 | 1d | 7 | 0
Eye Disorders
Lacrimation increased | 5 | 0 | 4 | <1d | 4 | 0
Vascular Disorders
Hot flushb | 5 | 0 | 2 | 0 | 6 | 0
Respiratory, Thoracic, and Mediastinal Disorders
Dyspneab | 7 | 1 | 4 | 1 | 9 | 1d
Coughb | 6 | 0 | 2 | 0 | 2 | 0
Gastrointestinal Disorders
Nausea | 53 | 3d | 40 | 2d | 42 | 2d
Vomitingb | 39 | 4d | 24 | 2 | 29 | 1d
Stomatitis/mucositisb | 31 | 4 | 20 | 3d | 29 | 6
Diarrheab | 44 | 6d | 39 | 9 | 22 | 1d
Constipation | 22 | 0 | 6 | <1d | 16 | 2d
Abdominal painb | 24 | 2d | 14 | 1d | 13 | 2d
Gastroesophageal reflux diseaseb | 7 | 1d | 8 | 0 | 6 | 0
Skin and Subcutaneous Tissue Disorders
Alopeciab | 31 | 0 | 3 | 0 | 48 | 0
Skin rashb | 17 | 1d | 7 | 0 | 9 | 2d
Nail disorderb | 24 | 2d | 10 | <1d | 9 | 0
Palmar-plantar erythrodysesthesia syndromeb | 64 | 18d | 63 | 17d | 8 | 2d
Pruritus | 5 | 0 | 2 | 0 | 6 | 1d
Skin exfoliationb | 5 | <1d | 3 | 0 | 2 | 0
Skin hyperpigmentationb | 11 | 0 | 14 | 0 | 2 | 0
Musculoskeletal, Connective Tissue, and Bone Disorders
Myalgia/arthralgiab | 39 | 8d | 5 | <1d | 49 | 8d
Musculoskeletal painb | 23 | 2d | 5 | 0 | 20 | 3d
General Disorders and Administration Site Conditions
Fatigue/astheniab | 60 | 16 | 29 | 4 | 56 | 13
Edemab | 8 | 0 | 5 | <1d | 9 | 1d
Pyrexia | 10 | 1d | 4 | 0 | 8 | 1d
Painb | 9 | 1d | 2 | 0 | 8 | 3d
Chest painb | 4 | 1d | <1 | 0 | 5 | 1d
Investigations
Weight decreased | 11 | 0 | 3 | 0 | 6 | 0
b A composite of multiple terms.
c Three patients (1 %) experienced Grade 5 (fatal) febrile neutropenia. Other neutropenia-related deaths (9) occurred in the absence of reported febrile neutropenia [see Warnings and Precautions (5.2)].
d No grade 4 reports.
e Peripheral sensory neuropathy was defined as the occurrence of any of the following: areflexia, burning sensation, dysesthesia, hyperesthesia, hypoesthesia, hyporeflexia, neuralgia, neuritis, neuropathy, neuropathy peripheral, neurotoxicity, painful response to normal stimuli, paresthesia, pallanesthesia, peripheral sensory neuropathy, polyneuropathy, polyneuropathy toxic and sensorimotor disorder.
Peripheral motor neuropathy was defined as the occurrence of any of the following: multifocal motor neuropathy, neuromuscular toxicity, peripheral motor neuropathy, and peripheral sensorimotor neuropathy.
f Palmar-plantar erythrodysesthesia (hand-foot syndrome) was graded on a 1 -3 severity scale in Study 046.

Table 5: Hematologic Abnormalities in Patients with Metastatic or Locally Advanced Breast Cancer Treated with IXEMPRA
 | Study 046 |  |  |  | Study 081
 | IXEMPRA with capecitabine n=369 |  | Capecitabine n=368 |  | IXEMPRA single agent n=126
Hematology Parameter | Grade 3 (%) | Grade 4 (%) | Grade 3 (%) | Grade 4 (%) | Grade 3 (%) | Grade 4 (%)
Neutropeniaa | 32 | 36 | 9 | 2 | 31 | 23
Leukopenia (WBC) | 41 | 16 | 5 | 1 | 36 | 13
Anemia (Hgb) | 8 | 2 | 4 | 1 | 6 | 2
Thrombocytopenia | 5 | 3 | 2 | 2 | 5 | 2
aG-CSF (granulocyte colony stimulating factor) or GM-CSF (granulocyte macrophage colony stimulating factor) was used in 20% and 17% of patients who received IXEMPRA in Study 046 and Study 081, respectively.

The following serious adverse reactions were also reported in 1323 patients treated with IXEMPRA as single agent or in combination with other therapies in clinical studies.

Infections and Infestations: sepsis, pneumonia, infection, neutropenic infection, urinary tract infection, bacterial infection, enterocolitis, laryngitis, lower respiratory tract infection

Blood and Lymphatic System Disorders: coagulopathy, lymphopenia

Metabolism and Nutrition Disorders: hyponatremia, metabolic acidosis, hypokalemia, hypovolemia

Nervous System Disorders: cognitive disorder, syncope, cerebral hemorrhage, abnormal coordination, lethargy

Cardiac Disorders: myocardial infarction, supraventricular arrhythmia, left ventricular dysfunction, angina pectoris, atrial flutter, cardiomyopathy, myocardial ischemia

Vascular Disorders: hypotension, thrombosis, embolism, hemorrhage, hypovolemic shock, vasculitis

Respiratory, Thoracic, and Mediastinal Disorders: pneumonitis, hypoxia, respiratory failure, acute pulmonary edema, dysphonia, pharyngolaryngeal pain

Gastrointestinal Disorders: ileus, colitis, impaired gastric emptying, esophagitis, dysphagia, gastritis, gastrointestinal hemorrhage

Hepatobiliary Disorders: acute hepatic failure, jaundice

Skin and Subcutaneous Tissue Disorders: erythema multiforme

Musculoskeletal, Connective Tissue, and Bone Disorders: muscular weakness, muscle spasms, trismus

Renal and Urinary Disorders: nephrolithiasis, renal failure

General Disorders and Administration Site Conditions: chills

Investigations: increased transaminases, increased blood alkaline phosphatase, increased gamma-glutamyltransferase

6.2 Postmarketing Experience

The following adverse reaction has been identified during postapproval use of IXEMPRA. Because these reactions are reported voluntarily from a population of uncertain size, it is not always possible to reliably estimate the frequency or establish a causal relationship to drug exposure.

Procedural Complications: Radiation recall

7 DRUG INTERACTIONS

7.1 Effect of Other Drugs on IXEMPRA

Strong CYP3A4 Inhibitors

The coadministration of IXEMPRA with a strong CYP3A4 inhibitor increased ixabepilone plasma concentration, which may increase the incidence and severity of adverse reactions of IXEMPRA. Avoid coadministration of IXEMPRA with strong CYP3A4 inhibitors. If the coadministration of IXEMPRA with strong CYP3A4 cannot be avoided, reduce the dose of IXEMPRA [see Dosage and Administration (2.5), Clinical Pharmacology (12.3].

Moderate or Weak CYP3A4 Inhibitors

The coadministration of IXEMPRA with moderate or weak CYP3A4 inhibitors may increase the incidence and severity of adverse reactions of IXEMPRA. Monitor for adverse reactions and reduce the dose of IXEMPRA as recommended [see Dosage and Administration (2.5), Adverse Reactions (6)].

Strong CYP3A4 Inducers

The coadministration of IXEMPRA with a strong CYP3A4 inducer, decreased plasma concentrations of ixabepilone, which may decrease the efficacy of IXEMPRA [see Clinical Pharmacology (12.3)]. Avoid the coadministration IXEMPRA with strong CYP3A4 inducers. If the coadministration of IXEMPRA with a strong CYP3A4 inducer cannot be avoided, increase the dose of IXEMPRA [see Dosage and Administration (2.4)].

Concomitant Use of IXEMPRA and Capecitabine

No clinically meaningful differences in the pharmacokinetics of ixabepilone and capecitabine were observed when IXEMPRA was administered in combination with capecitabine (1000 mg/m^2) [see Clinical Pharmacology (12.3)].

7.2 Effect of Ixabepilone on Other Drugs

Ixabepilone does not inhibit CYP enzymes at relevant clinical concentrations and is not expected to alter the plasma concentrations of other drugs [see Clinical Pharmacology (12.3)].

7.3 Capecitabine

In patients with cancer who received ixabepilone (40 mg/m^2) in combination with capecitabine (1000 mg/m^2), ixabepilone Cmax decreased by 19%, capecitabine Cmax decreased by 27%, and 5-fluorouracil AUC increased by 14%, as compared to ixabepilone or capecitabine administered separately. The interaction is not clinically significant given that the combination treatment is supported by efficacy data.

8 USE IN SPECIFIC POPULATIONS

8.1 Pregnancy

Risk Summary

Based on findings in animals and its mechanism of action, IXEMPRA can cause fetal harm when administered to a pregnant woman [see Clinical Pharmacology (12.1)]. There are no available data on the use of IXEMPRA in pregnant women to inform the drug-associated risk. IXEMPRA contains alcohol which can interfere with neurobehavioral development [see Clinical Considerations]. In animal reproduction studies, intravenous administration of ixabepilone to pregnant rats and rabbits during the period of organogenesis caused maternal toxicity, embryo-fetal lethality, and fetal abnormalities at maternal exposures below the human clinical exposure based on AUC (see Data). Advise females of reproductive potential and pregnant women of the potential risk to a fetus.

The background risk of major birth defects and miscarriage for the indicated population is unknown. In the U.S. general population, the estimated background risk of major birth defects and miscarriage in clinically recognized pregnancies is 2% to 4% and 15% to 20%, respectively.

Clinical Considerations

IXEMPRA contains alcohol [see Warnings and Precautions (5.7)]. Published studies have demonstrated that alcohol is associated with fetal harm including central nervous system abnormalities, behavioral disorders, and impaired intellectual development.

Data

Animal data

In embryo-fetal development studies, pregnant rats and rabbits received intravenous doses of 0.02, 0.08, and 0.3 mg/kg/day and 0.01, 0.03, 0.11, and 0.3 mg/kg/day, respectively during the period of organogenesis. In rats, an increase in resorptions and post-implantation loss and a decrease in the number of live fetuses and fetal weight was observed at the maternally toxic dose of 0.3 mg/kg/day (approximately 0.1 times the human clinical exposure based on AUC). Abnormalities included a reduced ossification of caudal vertebrae, sternebrae, and metacarpals. In rabbits, ixabepilone caused maternal toxicity (death) and embryo-fetal toxicity (resorptions) at 0.3 mg/kg/day (approximately 0.1 times the human clinical dose based on body surface area).

8.2 Lactation

Risk Summary

There is no data on the presence of IXEMPRA in human milk, the effects on the breastfed child, or the effects on milk production. Ixabepilone and/or its metabolites were present in milk of lactating rats (see Data). Because of the potential for serious adverse reactions in a breastfed child, advise women not to breastfeed during treatment with IXEMPRA and for 2 weeks after the last dose.

Data

Animal data

Following intravenous administration of radiolabeled ixabepilone to rats on days 7 to 9 postpartum, concentrations of radioactivity in milk were comparable with those in plasma and declined in parallel with the plasma concentrations.

8.3 Females and Males of Reproductive Potential

Based on findings in animals and its mechanism of action, IXEMPRA can cause fetal harm when administered to a pregnant woman [see Use in Specific Populations (8.1)].

Pregnancy Testing

Verify the pregnancy status of females of reproductive potential prior to initiating treatment with IXEMPRA.

Contraception

Females

Advise females of reproductive potential to use effective contraception during treatment with IXEMPRA and for 7 months after the last dose.

Males

Based on genotoxicity and animal studies, advise male patients with female partners of reproductive potential to use effective contraception during treatment with IXEMPRA and for 4 months after the last dose [see Nonclinical Toxicology (13.1)].

Infertility

Based on findings in animals, IXEMPRA may impair male and female fertility [see Nonclinical Toxicology (13.1)].

.

8.4 Pediatric Use

The alcohol content of IXEMPRA should be taken into account when given to pediatric patients [see Warnings and Precautions (5.6)].

The safety and effectiveness of IXEMPRA in pediatric patients have not been established. Safety and efficacy were assessed, but not established for IXEMPRA across two studies: an open-label, dose-finding trial in 21 patients aged 2 to 18 years with advanced or refractory solid tumors and hematologic malignancies [NCT00030108] and a trial with 28 patients aged 3 to 18 years with advanced or refractory solid tumors [NCT00331643] that was terminated early due to lack of efficacy. No new safety signals were identified. The median BSA normalized clearance of ixabepilone in 16 patients aged 2 to 18 years (17 L/h/m^2) was within range of that of patients greater than 18 years (20 L/h/m^2).

8.5 Geriatric Use

Clinical studies of IXEMPRA did not include sufficient numbers of patients aged sixty-five and over to determine whether they respond differently from younger patients.

Of the 431 patients treated with IXEMPRA in combination with capecitabine, 10% were 65 years of age and over, and 0.1% were 75 years of age and over. The incidence of grade 3/4 adverse reactions was higher in patients ³65 years of age versus those <65 years of age (82% versus 68%) including grade 3/4 stomatitis (9% versus 1%), diarrhea (9% versus 6%), palmar-plantar erythrodysesthesia syndrome (27% versus 20%), peripheral neuropathy (24% versus 22%), febrile neutropenia (9% versus 3%), fatigue (16% versus 12%), and asthenia (11% versus 6%). Deaths due to adverse reactions occurred in 2 (4.7%) of 43 patients ³65 years with normal baseline hepatic function or mild impairment.

Of the 240 patients with breast cancer treated with IXEMPRA as a single agent, 13% were 65 years of age and over, and 0.2% were 75 years of age and over.

8.6 Hepatic Impairment

Monitor hepatic function before initiation of IXEMPRA and periodically thereafter.

Dose reduction is recommended when administering IXEMPRA as a single agent to patients with hepatic impairment [see Dosage and Administration (2.4)].

IXEMPRA in combination with capecitabine is contraindicated in patients with AST or ALT >2.5 x ULN or bilirubin >1 x ULN [see Contraindications (4)].

The alcohol content of IXEMPRA should be taken into account when given to patients with hepatic impairment [see Warnings and Precautions (5.7)].

10 OVERDOSAGE

In patients who received an overdosage of IXEMPRA of up to 100 mg/m^2 (approximately 2.5 times the recommended dosage), peripheral neuropathy, fatigue, musculoskeletal pain/myalgia, and gastrointestinal symptoms (nausea, anorexia, diarrhea, abdominal pain, stomatitis) occurred.

There is no known antidote for overdosage of IXEMPRA. In case of overdosage, closely monitor patients for adverse reactions and provide supportive treatment as clinically indicated.

11 DESCRIPTION

IXEMPRA (ixabepilone) is a microtubule inhibitor belonging to a class of antineoplastic agents, the epothilones and their analogs. The epothilones are isolated from the myxobacterium Sorangium cellulosum. Ixabepilone is a semisynthetic analog of epothilone B, a 16-membered polyketide macrolide, with a chemically modified lactam substitution for the naturally existing lactone.

The chemical name for ixabepilone is (1 S,3 S,7 S,10 R,11 S,12 S,16 R)-7,11 -dihydroxy-8,8,10,12,16-pentamethyl-3- [(1 E)-1 -methyl-2-(2-methyl-4-thiazolyl)ethenyl]-17-oxa-4-azabicyclo[14.1.0] heptadecane-5,9-dione, and it has a molecular weight of 506.7. Ixabepilone has the following structural formula:

IXEMPRA (ixabepilone) for injection is intended for intravenous infusion only after constitution with the supplied DILUENT and after further dilution with a specified infusion fluid [see dosage (2.)]. IXEMPRA (ixabepilone) for injection is supplied as a sterile, non-pyrogenic, single-dose vial providing 15 mg or 45 mg ixabepilone as a lyophilized white powder. The DILUENT for IXEMPRA is a sterile, non-pyrogenic, solution of 52.8% (w/v) purified polyoxyethylated castor oil and 39.8% (w/v) dehydrated alcohol, USP. The IXEMPRA (ixabepilone) for injection and the DILUENT for IXEMPRA are copackaged and supplied as IXEMPRA Kit

12 CLINICAL PHARMACOLOGY

12.1 Mechanism of Action

Ixabepilone is a semi-synthetic analog of epothilone B. Ixabepilone binds directly to β-tubulin subunits on microtubules, leading to suppression of microtubule dynamics. Ixabepilone suppresses the dynamic instability of αβ-II and αβ-III microtubules. Ixabepilone possesses low in vitro susceptibility to multiple tumor resistance mechanisms including efflux transporters, such as MRP-1 and P-glycoprotein (P-gp). Ixabepilone blocks cells in the mitotic phase of the cell division cycle, leading to cell death.

12.2 Pharmacodynamics

Ixabepilone has a plasma concentration-dependent effect on tubulin dynamics in peripheral blood mononuclear cells that is observed as the formation of microtubule bundles.

Cardiac Electrophysiology

At the recommended dosage, IXEMPRA does not cause large mean increases (i.e., >20 msec) in the QT interval. The QT prolongation potential of ixabepilone was assessed as part of an uncontrolled, open-label, single-dose study in advanced cancer patients. Fourteen patients received a single dose of IXEMPRA 40 mg/m2 intravenously over 3 hours and serial ECGs were collected over 24 hours. The maximum mean ΔQTcF was observed 1 hour after the end of infusion and was 8 ms (upper 95% CI: 12 ms). No patients had a QTcF interval >450 ms or ΔQTcF >30 ms after IXEMPRA administration. However, small increases in QTc interval with the use of ixabepilone cannot be excluded due to study design limitations

12.3 Pharmacokinetics

Following administration of a single 40 mg/m^2 dose of IXEMPRA, the mean (% coefficient of variation) maximum plasma concentration (Cmax) was 252 ng/mL (56%), and the mean (%CV) area under the curve (AUC) was 2,143 ng·hr/mL (48%). The pharmacokinetics of ixabepilone were linear at doses of 15 (0.375 times the approved recommended dosage) to 57 mg/m^2 (1.425 times the approved recommended dosage).

Distribution

The mean (%CV) volume of distribution at steady-state was greater than1,000 L (x CV%). Serum protein binding of ixabepilone ranged from 67% to 77% and the blood-to-plasma concentration ratios ranged from 0.65 to 0.85.

Elimination

Ixabepilone has a terminal elimination half-life of approximately 52 hours (x CV%).

Metabolism

Ixabepilone is metabolized by CYP3A4.

Excretion

Ixabepilone is eliminated primarily as metabolites in feces (65% of the dose) and in urine (21% of the dose). Unchanged ixabepilone accounted for approximately 1.6% and 5.6% of the dose in feces and urine, respectively.

Specific Populations

Based upon a population pharmacokinetic analysis in 676 cancer patients, gender, race, age, mild and moderate renal insufficiency (creatinine clearance [CLcr]CrCL >30 mL/min) do not have clinically meaningful effects on the pharmacokinetics of ixabepilone.

Patients with Hepatic Impairment

IXEMPRA was evaluated in 56 patients with mild to severe hepatic impairment defined by bilirubin levels and AST levels. Compared to patients with normal hepatic function (n=17), the area under the curve (AUC0-infinity) of ixabepilone AUC increased by:

- 22% in patients with mild hepatic impairment [a) bilirubin >1 to 1.5 x ULN and AST < ULN or b) AST >ULN but bilirubin <1.5 x ULN];
- 30% in patients with moderate hepatic impairment (bilirubin >1.5 to 3 x ULN and any AST level);
- 81% in patients with severe hepatic impairment (bilirubin >3 x ULN and any AST level).

Drug Interaction Studies

Clinical Studies

Effect of Strong CYP3A4 Inhibitors on IXEMPRA:

Coadministration of ixabepilone with ketoconazole, a strong CYP3A4 inhibitor, increased ixabepilone AUC by 79% compared to ixabepilone treatment alone.

Effect of Strong CYP3A4 Inducers on IXEMPRA:

Coadministration of IXEMPRA with rifampin, a strong CYP3A4 inducer, decreased ixabepilone AUC by 43% compared to IXEMPRA treatment alone.

Capecitabine:

In patients with cancer who received ixabepilone (40 mg/m^2) in combination with capecitabine decreased (1000 mg/m^2), ixabepilone Cmax decreased by 19% and capecitabine Cmax decreased by 27%, and 5-fluorouracil AUC increased by 14%; as compared to ixabepilone or capecitabine administered separately.

In Vitro Studies

Cytochrome P450 (CYP) Enzymes:

In vitro studies using human liver microsomes indicate that clinically relevant concentrations of ixabepilone do not inhibit CYP3A4, CYP1A2, CYP2A6, CYP2B6, CYP2C8, CYP2C9, CYP2C19, or CYP2D6.

Ixabepilone does not induce the activity or the corresponding mRNA levels of CYP1A2, CYP2B6, CYP2C9, or CYP3A4 in cultured human hepatocytes at clinically relevant concentrations.

Transporter Systems:

Ixabepilone is a substrate of P-gp but is not a substrate of BCRP. Ixabepilone is an inhibitor of P-gp for the drug efflux transporter P‑glycoprotein (P-gp).

13 NONCLINICAL TOXICOLOGY

13.1 Carcinogenesis, Mutagenesis, Impairment of Fertility

Carcinogenicity studies with ixabepilone have not been conducted. Ixabepilone did not induce mutations in the microbial mutagenesis (Ames) assay and was not clastogenic in an in vitro cytogenetic assay using primary human lymphocytes. Ixabepilone was clastogenic (induction of micronuclei) in the in vivo rat micronucleus assay at doses ≥0.625 mg/kg/day.

There were no effects on male or female rat mating or fertility at doses up to 0.2 mg/kg/day in both males and females (approximately 0.1 times the expected human clinical exposure based on AUC). The effect of ixabepilone on human fertility is unknown. However, when rats were given an IV infusion of ixabepilone during breeding and through the first 7 days of gestation, a significant increase in resorptions and pre- and post-implantation loss and a decrease in the number of corpora lutea was observed at 0.2 mg/kg/day. Testicular atrophy or degeneration was observed in 6-month rat and 9-month dog studies when ixabepilone was given every 21 days at intravenous doses of 6.7 mg/kg (40 mg/m^2) in rats (approximately 2.1 times the expected clinical exposure based on AUC) and 0.5 and 0.75 mg/kg (10 and 15 mg/m^2) in dogs (approximately 0.2 and 0.4 times the expected clinical exposure based on AUC).

13.2 Animal Toxicology and/or Pharmacology

Overdosage

In rats, single intravenous doses of ixabepilone from 60 to 180 mg/m^2 (mean AUC values ≥8156ng·h/mL) were associated with mortality occurring between 5 and 14 days after dosing, and toxicity was principally manifested in the gastrointestinal, hematopoietic (bone-marrow), lymphatic, peripheral-nervous, and male-reproductive systems. In dogs, a single intravenous dose of 100 mg/m^2 (mean AUC value of 6925 ng·h/mL) was markedly toxic, inducing severe gastrointestinal toxicity and death 3 days after dosing.

14 CLINICAL STUDIES

Combination Therapy

In an open-label, multicenter, multinational, randomized trial of 752 patients with metastatic or locally advanced breast cancer, the efficacy and safety of IXEMPRA (40 mg/m^2 every 3 weeks) in combination with capecitabine (at 1000 mg/m^2 twice daily for 2 weeks followed by 1 week rest) were assessed in comparison with capecitabine as a single agent (at 1250 mg/m^2 twice daily for 2 weeks followed by 1 week rest). Patients were previously treated with anthracyclines and taxanes. Patients were required to have demonstrated tumor progression or resistance to taxanes and anthracyclines as follows:

- tumor progression within 3 months of the last anthracycline dose in the metastatic setting or recurrence within 6 months in the adjuvant or neoadjuvant setting, and
- tumor progression within 4 months of the last taxane dose in the metastatic setting or recurrence within 12 months in the adjuvant or neoadjuvant setting.

For anthracyclines, patients who received a minimum cumulative dose of 240 mg/m^2 of doxorubicin or 360 mg/m^2 of epirubicin were also eligible.

In this study, the median age of patients was 53 years, 67% were White, 23% were Asian, and 3% were Black; Karnofsky performance status was 70-100%, and 75% had received prior adjuvant or neo-adjuvant chemotherapy. Tumors were ER-positive in 47% of patients, ER-negative in 43%, HER2-positive in 15%, HER2-negative in 61%, and ER-negative, PR-negative, HER2-negative in 25%. The baseline disease characteristics and previous therapies for all patients (n=752) are shown in Table 6.

Table 6: Baseline Disease Characteristics and Previous Therapies
 | IXEMPRA with capecitabine n=375 | Capecitabine n=377
Site of disease
Visceral disease (liver or lung) | 316(84%) | 315 (84%)
Liver | 245 (65%) | 228(61%)
Lung | 180(48%) | 174 (46%)
Lymph node | 250 (67%) | 249 (66%)
Bone | 168(45%) | 162 (43%)
Skin/soft tissue | 60(16%) | 62(16%)
Number of prior chemotherapy regimens in metastatic settinga
0 | 27 (7%) | 33 (9%)
1 | 179(48%) | 184(49%)
2 | 152(41%) | 138(37%)
≥3 | 17 (5%) | 22 (6%)
Anthracycline resistanceb | 164(44%) | 165 (44%)
Taxane Resistancec
Neoadjuvant/adjuvant setting | 40(11%) | 44(12%)
Metastatic setting | 327 (87%) | 319 (85%)
aFor IXEMPRA plus capecitabine versus capecitabine only, prior treatment in the metastatic setting included cyclophosphamide (25% vs. 23%), fluorouracil (22% vs. 16%), vinorelbine (11% vs. 12%), gemcitabine (9% each arm), carboplatin (9% vs. 7%), liposomal doxorubicin (3% each arm), and cisplatin (2% vs. 3%).
b Tumor progression within 3 months in the metastatic setting or recurrence within 6 months in the adjuvant or neoadjuvant setting.
c 24% and 21% of patients had received 2 or more taxane-containing regimens in the combination and single agent treatment groups, respectively.

The patients in the combination treatment group received a median of 5 cycles of treatment and patients in the capecitabine single-agent treatment group received a median of 4 cycles of treatment.

The major efficacy outcome measures of the study was progression-free survival (PFS) defined as time from randomization to radiologic progression as determined by Independent Radiologic Review (IRR), clinical progression of measurable skin lesions or death from any cause. Additional efficacy outcome measures included objective tumor response based on Response Evaluation Criteria in Solid Tumors (RECIST), response duration, and overall survival.

IXEMPRA in combination with capecitabine resulted in a statistically significant improvement in PFS compared to capecitabine. The results of the study are presented in Table 7 and Figure 1.

Table 7: Efficacy of IXEMPRA in Combination with Capecitabine vs Capecitabine Alone - Intent-to-Treat Analysis
Efficacy Parameter | IXEMPRA with capecitabine n=375 | Capecitabine n=377
PFS
Number of events | 242 | 256
Median | 5.7 months | 4.1 months
(95% Cl) | (4.8 - 6.7) | (3.1 - 4.3)
Hazard Ratio (95% Cl) | 0.69 (0.58 - 0.83)
p-valuea (Log rank) | <0.0001
Objective Tumor Response Rate | 34.7% | 14.3%
(95% Cl) | (29.9 - 39.7) | (10.9 -18.3)
p-valuea,b (CMH) | <0.0001
Duration of Response, Median | 6.4 months | 5.6 months
(95% Cl) | (5.6 - 7.1) | (4.2 - 7.5)
a Stratified by visceral metastasis in liver/lung, prior chemotherapy in metastatic setting, and anthracycline resistance.
b Cochran-Mantel-Haenszel test

Figure 1: Progression-free Survival Kaplan Meier Curves

There was no statistically significant difference in overall survival between treatment arms in this study, as well as in a second similar study. In the study described above, the median overall survivals were 12.9 months (95% Cl: 11.5, 14.2) in the combination therapy arm and 11.1 months (95% Cl: 10.0,12.5) in the capecitabine alone arm [Hazard Ratio 90 (95% Cl: 0.77,1.05), p-value=0.19j.

In the second trial, comparing IXEMPRA in combination with capecitabine versus capecitabine alone, conducted in 1221 patients pretreated with an anthracycline and a taxane, the median overall survival was 16.4 months (95% Cl: 15.0,17.9) in the combination therapy arm and 15.6 months (95% Cl: 13.9,17.0), in the capecitabine alone arm [Hazard Ratio 0.90 (95% Cl: 0.78,1.03), p-value=0.12.

IXEMPRA as a Single Agent

IXEMPRA was evaluated as a single agent in a multicenter single-arm study in 126 women with metastatic or locally advanced breast cancer. The study enrolled patients whose tumors had recurred or had progressed following two or more chemotherapy regimens including an anthracycline, a taxane, and capecitabine. Patients who had received a minimum cumulative dose of 240 mg/m^2 of doxorubicin or 360 mg/m^2 of epirubicin were also eligible. Tumor progression or recurrence were prospectively defined as follows:

- Disease progression while on therapy in the metastatic setting (defined as progression while on treatment or within 8 weeks of last dose),
- Recurrence within 6 months of the last dose in the adjuvant or neoadjuvant setting (only for anthracycline and taxane),
- HER2-positive patients must also have progressed during or after discontinuation of trastuzumab.

In this study, the median age was 51 years (range, 30-78), and 79% were White, 5% Black, and 2% Asian, Kamofsky performance status was 70-100%, 88% had received two or more prior chemotherapy regimens for metastatic disease, and 86% had liver and/or lung metastases. Tumors were ER-positive in 48% of patients, ER-negative in 44%, HER2-positive in 7%, HER2-negative in 72%, and ER-negative, PR-negative, HER2-negative in 33%.

IXEMPRA was administered at a dose of 40 mg/m^2 intravenously over 3 hours every 3 weeks. Patients received a median of 4 cycles (range 1 to 18) of IXEMPRA therapy.

Objective tumor response was determined by independent radiologic and investigator review using RECIST. Efficacy results are presented in Table 8.

Table 8: Efficacy of IXEMPRA in Metastatic and Locally Advanced Breast Cancer
Endpoint | Result
Objective tumor response rate (95% Cl)
- IRR Assessmenta (n=113) - Investigator Assessment (n=126) | 12.4% (6.9 -19.9) 18.3% (11.9-26.1)
Time to responseb (n=14)
- Median, weeks (min - max) | 6.1 (5 - 54.4)
Duration of responseb (n=14)
- Median, months (95% Cl) | 6.0 (5.0 - 7.6)
a All responses were partial.
b As assessed by IRR.

15 REFERENCES

1. OSHA Hazardous Drugs. OSHA. http://www.osha.gov/SLTC/hazardousdrugs/index.html OSHA

16 HOW SUPPLIED/STORAGE AND HANDLING

IXEMPRA is supplied as a Kit containing one single-dose vial of IXEMPRA® (ixabepilone) for injection and one vial of DILUENT for IXEMPRA.

NDC 70020-1910-1 | IXEMPRA® Kit containing one single-dose vial of IXEMPRA® (ixabepilone) for injection, 15 mg and one vial of DILUENT for IXEMPRA, 8 mL
NDC 70020-1911 -1 | IXEMPRA® Kit containing one single-dose vial of IXEMPRA® (ixabepilone) for injection, 45 mg and one vial of DILUENT for IXEMPRA, 23.5 mL

IXEMPRA Kit must be stored in a refrigerator at 2° C to 8° C (36° F to 46° F). Retain in original package until time of use to protect from light.

IXEMPRA is a hazardous drug. Follow applicable special handling and disposal procedures.^1

17 PATIENT COUNSELING INFORMATION

Advise the patient to read the FDA-approved patient labeling

17.1 Peripheral Neuropathy

Advice patients to report any numbness and tingling of the hands or feet to their healthcare provider [see Warnings and Precautions (5.1)].

17.2 Fever/Neutropenia

Instruct patients to immediately contact their healthcare provider if a fever of 100.5° F or greater or other evidence of potential infection such as chills, cough, or burning or pain on urination occur [see Warnings and Precautions (5.2)].

17.3 Hypersensitivity Reactions

Advise patients to immediately contact their healthcare provider if they experience urticaria, pruritus, rash, flushing, swelling, dyspnea, chest tightness, or other hypersensitivity-related symptoms following an infusion of IXEMPRA [see Warnings and Precautions (5.4)].

17.4 Cardiac Adverse Reactions

Advise patients to immediately contact call their healthcare provider if they experience chest pain, difficulty breathing, palpitations, or unusual weight gain [see Warnings and Precautions (5.5)].

17.5 Embryo-Fetal Toxicity

Advise females of reproductive potential and pregnant women of the potential risk to a fetus. Advise patients to inform their healthcare provider of a known or suspected pregnancy.

Advise females of reproductive potential to use effective contraception during treatment with IXEMPRA and for 7 months after the last dose. Advise male patients with female partners of reproductive potential to use effective contraception during treatment with IXEMPRA and for 4 months after the last dose [see Warnings and Precautions (5.6) and Use in Specific Populations (8.1, 8.3)].

17.6 Lactation

Advise women not to breastfeed during treatment with IXEMPRA and for 2 weeks after the last dose [see Use in Specific Populations (8.2)].

17.7 Infertility

Advise males and females of reproductive potential that IXEMPRA may impair fertility [see Use in Specific Populations (8.2)].

17.8 Alcohol Content in IXEMPRA

Explain to patients the possible effects of the alcohol content in IXEMPRA, including possible effects on the central nervous system [see Warnings and Precautions (5.7)].

FDA-Approved Patient Labeling

Patient Information

IXEMPRA® Kit

(ĭk-'sĕm-pră)

(ixabepilone)

for injection, for intravenous use

What is the most important information I should know about IXEMPRA?

Your healthcare provider should do blood tests to check your liver function:

- before you begin receiving IXEMPRA
- as needed while you are receiving IXEMPRA

If blood tests show that you have liver problems, do not receive injections of IXEMPRA along with the medicine capecitabine. Taking these two medicines together if you have liver problems increases your chance of serious problems. These include serious infection and death due to a very low white blood cell count (neutropenia).

What is IXEMPRA?

IXEMPRA is used alone or with another cancer medicine called capecitabine to treat locally advanced breast cancer or breast cancer that has spread to other parts of the body (metastatic), when certain other medicines have not worked or no longer work.

It is not known if IXEMPRA is safe and effective in children.

Do not receive IXEMPRA if you:

- have low white blood cell or platelet counts. Your healthcare provider will check your blood counts.
- are allergic to a medicine, such as TAXOL®, that contains Cremophor® EL or polyoxyethylated castor oil..
- are also taking a cancer medicine called capecitabine and you have liver problems. See “What is the most important information I should know about IXEMPRA?”

Before you receive IXEMPRA, tell your healthcare provider about all of your medical conditions, including if you:

- have liver problems
- have heart problems or a history of heart problems
- have had an allergic reaction to IXEMPRA. You will receive medicines before each injection of IXEMPRA to decrease the chance of an allergic reaction. See “How will I receive IXEMPRA?”

are pregnant or plan to become pregnant. IXEMPRA can harm your unborn baby. Tell your healthcare provider right away if you become pregnant or think you are pregnant during treatment with IXEMPRA.

- o If you are able to become pregnant, your healthcare provider should do a pregnancy test before you start treatment with IXEMPRA.
- o Females who are able to become pregnant should use effective birth control during treatment with IXEMPRA and for 7 months after the last dose.
- o Males with female partners who are able to become pregnant should use effective birth control during treatment with IXEMPRA and for 4 months after the last dose.

· are breastfeeding or plan to breastfeed. It is not known if IXEMPRA passes into breast milk. Do not breastfeed during treatment with IXEMPRA and for 2 weeks after the last dose.

Tell your healthcare provider about all the medicines you take, including prescription and over-the-counter medicines, vitamins, and herbal supplements.

IXEMPRA and certain other medicines may affect each other causing side effects. IXEMPRA may affect the way other medicines work, and other medicines may affect how IXEMPRA works.

Know the medicines you take. Keep a list of your medicines with you to show your healthcare provider.

How will I receive IXEMPRA?

IXEMPRA is given by an injection directly into your vein (intravenous infusion). IXEMPRA is usually given 1 time every 3 weeks. Each treatment with IXEMPRA will take about 3 hours.

Your healthcare provider will decide how much IXEMPRA you will receive and how often you will receive it.

To lower the chance of allergic reaction, you will receive other medicines about 1 hour before each treatment with IXEMPRA. See “What are the possible side effects of IXEMPRA?”

If you have an allergic reaction to IXEMPRA, you will receive a steroid medicine before future doses of IXEMPRA. You may also need to receive your doses of IXEMPRA more slowly.

What should I avoid while receiving IXEMPRA?

IXEMPRA contains alcohol. If you are dizzy or drowsy, avoid activities that may be dangerous, such as driving or operating machinery.

Do not drink grapefruit juice during treatment with IXEMPRA. Drinking grapefruit juice may cause you to have too much IXEMPRA in your blood and lead to side effects.

What are the possible side effects of IXEMPRA?

IXEMPRA may cause serious side effects including:

- Numbness, tingling, or burning in the hands or feet can occur during treatment with IXEMPRA peripheral neuropathy (PN). These symptoms may be new or get worse during treatment with IXEMPRA. If you have diabetes, you may have a higher risk for severe neuropathy. These symptoms often occur early during treatment with IXEMPRA. Tell your healthcare provider if you have any of these symptoms. Your dose of IXEMPRA may need to be decreased, stopped until your symptoms get better, or totally stopped.
- Low blood cell counts especially low white blood counts (neutropenia). Low white blood cell counts are common with IXEMPRA treatment, but can sometimes be severe and have led to death. White blood cells help protect the body from infections caused by bacteria. If you get a fever or infection when your white blood cells are very low, you can become seriously ill and die. You may need treatment in the hospital with antibiotic medicines. Your healthcare provider will monitor your white blood cell count often with blood tests. Tell your healthcare provider right away or go to the nearest hospital emergency room if you have a fever (temperature above 100.5° F) or other signs of infection, such as chills, cough, burning or pain when you urinate, any time between treatments with IXEMPRA.
- Allergic reactions. Severe allergic reactions can happen with IXEMPRA and may cause death in some cases. Allergic reactions are most likely to happen while IXEMPRA is being injected into your vein. Tell your healthcare provider right away if you get any of the following signs and symptoms of an allergic reaction:
  - itching, hives (raised itchy welts), rash
  - flushed face
  - sudden swelling of face, throat or tongue
  - chest tightness, trouble breathing
  - feel dizzy or faint
  - feel your heart beating (palpitations)
- Heart problems. IXEMPRA might cause decreased blood flow to the heart, problems with heart function, and abnormal heart beat. This is seen more often in patients who also take capecitabine. Tell your healthcare provider right away if you have any of the following symptoms:
  - chest pain
  - difficulty breathing
  - feel your heart beating (palpitations)
  - unusual weight gain

The most common side effects with IXEMPRA when used alone or with capecitabine may include:

- tiredness
- loss of appetite
- disorders of toenails and fingernails
- hair loss
- fever
- decreased red blood cell count (anemia)
- joint and muscle pain
- headache
- decreased platelet count (thrombocytopenia)
- nausea, vomiting, diarrhea, constipation, and abdominal pain
- sores on the lip, in the mouth and esophagus
- tender, red palms and soles of feet (hand-foot syndrome) that looks like a sunburn; the skin may become dry and peel. There may also be numbness and tingling.

IXEMPRA may cause fertility problems in females and males, which may affect your ability to have children. Talk to your healthcare provider if you have concerns about fertility.

These are not all of the possible side effects of IXEMPRA. Call your doctor for medical advice about side effects. You may report side effects to FDA at 1-800-FDA-1088.

General information about the safe and effective use of IXEMPRA

Medicines are sometimes prescribed for purposes other than those listed in a Patient Information leaflet. If you would like more information about IXEMPRA, talk with your healthcare provider. You can ask your healthcare provider or pharmacist for information about IXEMPRA that is written for health professionals.

What are the ingredients in IXEMPRA?

Active ingredient: ixabepilone

Inactive ingredients:The DILUENT for IXEMPRA contains purified polyoxyethylated castor oil and dehydrated alcohol.

IXEMPRA® (ixabepilone) for injection Manufactured by: Baxter Oncology GmbH, 33790 Halle/Westfalen, Germany

DILUENT for IXEMPRA Manufactured by: Baxter Oncology GmbH, 33790 Halle/ Westfalen, Germany

Distributed by R-Pharm US LLC, Princeton, NJ 08543 USA

R-PHARM US

RPH-00002

5645-0006

For more information about IXEMPRA, call 1-844-586-8953.

This Patient Information has been approved by the U.S. Food and Drug Administration. Revised January 2022

Principal Display Panel - Carton Label

Single dose vials NDC 70020-1910-1

IXEMPRA® Kit

(ixabepilone) for injection

15 mg Rx only

For intravenous infusion only

Each carton contains

1 vial IXEMPRA (ixabepilone)
for injection 15 mg

1 vial DILUENT for IXEMPRA 8 mL

Reconstitution and dilution required
(see insert).

Refrigerate

Distribute by

R-Pharm US LLC

Princeton, NJ 08543 USA

Principal Display Panel - Carton Label

Single dose vials NDC 70020-1911-1

IXEMPRA® Kit

(ixabepilone) for injection

45 mg Rx only

For intravenous infusion only

Each carton contains

1 vial IXEMPRA (ixabepilone)
for injection 15 mg

1 vial DILUENT for IXEMPRA 23.5 mL

Reconstitution and dilution required (see insert).

Refrigerate

Distribute by

R-Pharm US LLC

Princeton, NJ 08543 USA

Principal Display Panel - Vial Label

Single dose vial NDC 70020-1910-2

IXEMPRA®
(ixabepilone) for injection

15 mg Rx only

For intravenous infusion only

reconstitution and dilution required
(see insert).

Distributed by R-Pharm US LLC

Princeton, NJ 08543 USA

Principal Display Panel - Vial Label

Single dose vial NDC 70020-1911-2

IXEMPRA®
(ixabepilone) for injection

45 mg Rx only

For intravenous infusion only

Reconstitution and dilution required
(see insert).

Distributed by R-Pharm US LLC

Princeton, NJ 08543 USA

Principal Display Panel - Vial Label

Single dose vial NDC 70020-1265-1

DILUENT for
IXEMPRA ®
(ixabepilone) for injection

8 mL Rx only

Not for direct administration

Distributed by R-Pharm US LLC

Princeton, NJ 08543 USA

Principal Display Panel - Vial Label

Single dose vial NDC 70020-1266-2

DILUENT for
IXEMPRA ®
(ixabepilone) for injection

23.5 mL Rx only

Not for direct administration

Distributed by R-Pharm US LLC

Princeton, NJ 08543 USA